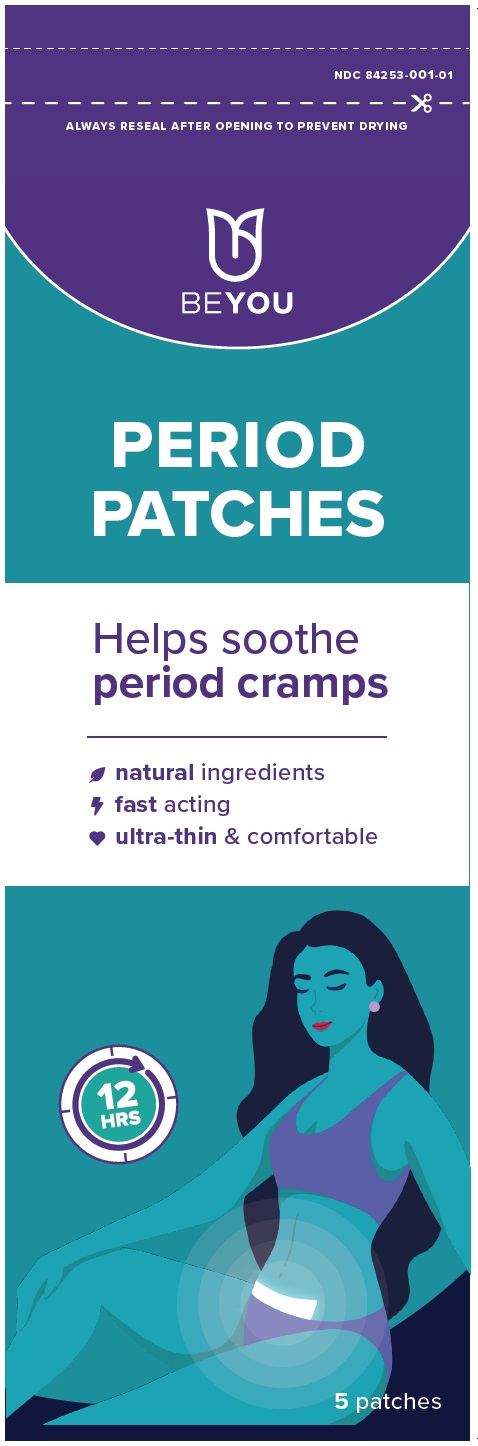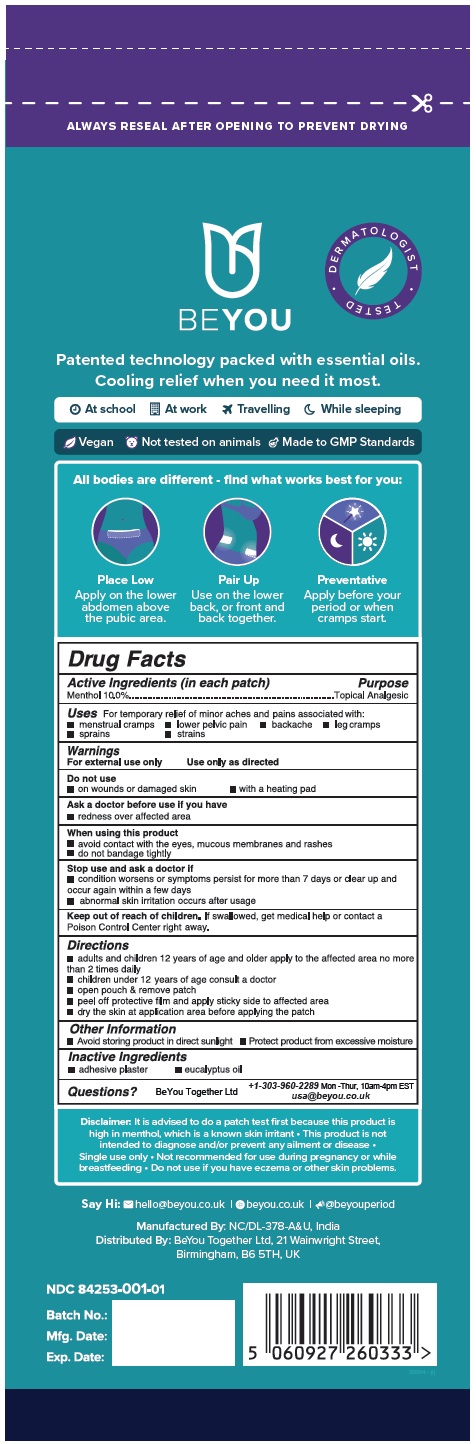 DRUG LABEL: FEMININE PAIN RELIEF
NDC: 84253-001 | Form: PATCH
Manufacturer: BeYou Together Ltd
Category: otc | Type: HUMAN OTC DRUG LABEL
Date: 20251231

ACTIVE INGREDIENTS: MENTHOL, UNSPECIFIED FORM 10 mg/1 1
INACTIVE INGREDIENTS: EUCALYPTUS OIL

BEYOU PERIOD PATCHES

DRUG FACTS

Active Ingredient Purpose

Menthol 10.0%.........................................................................Topical Analgesic

Uses

For temporary relief of minor aches and pains associated with:

- menstrual cramps
- lower pelvic pain
- backache
- leg cramps
- sprains
- strains

Warnings

For external use only
Use only as directed

Do Not Use

- on wounds or damaged skin
- with a heating pad

Ask a doctor before use if you have

- redness over affected area

When using this product

- avoid contact with eyes, mucous membranes and rashes
- do not bandage tightly

Stop use and ask a doctor if

- condition worsens or if symptoms persist for more than 7 days or clear up and occur again within a few days
- abnormal skin irritation occurs after usage

Keep out of reach of children.If swallowed, seek medical help or contact a Poison Control Center right away.

Directions

- adults and children 12 years of age and older apply to the affected area no more than 2 times daily
- children under 12 years of age consult a doctor
- open pouch & remove patch
- peel off protective film and apply sticky side to affected area
- dry the skin at application area before applying the patch

Other Information

- Avoid storing product in direct sunlight
- Protect product from excessive moisture

Inactive Ingredients

- adhesive Plaster
- eucalyptus oil

Questions?

+1-303-960-2289 Mon-Thur, 10am-4pm EST

usa@beyou.co.uk

Distributed By:
BeYou Together Ltd,
21 Wainwright Street,
Birmingham, B6 5TH, UK

Made in India.

PRINCIPAL DISPLAY PANEL

BEYOU Period Patches - NDC 84253-001-01 - 5 Patches Label